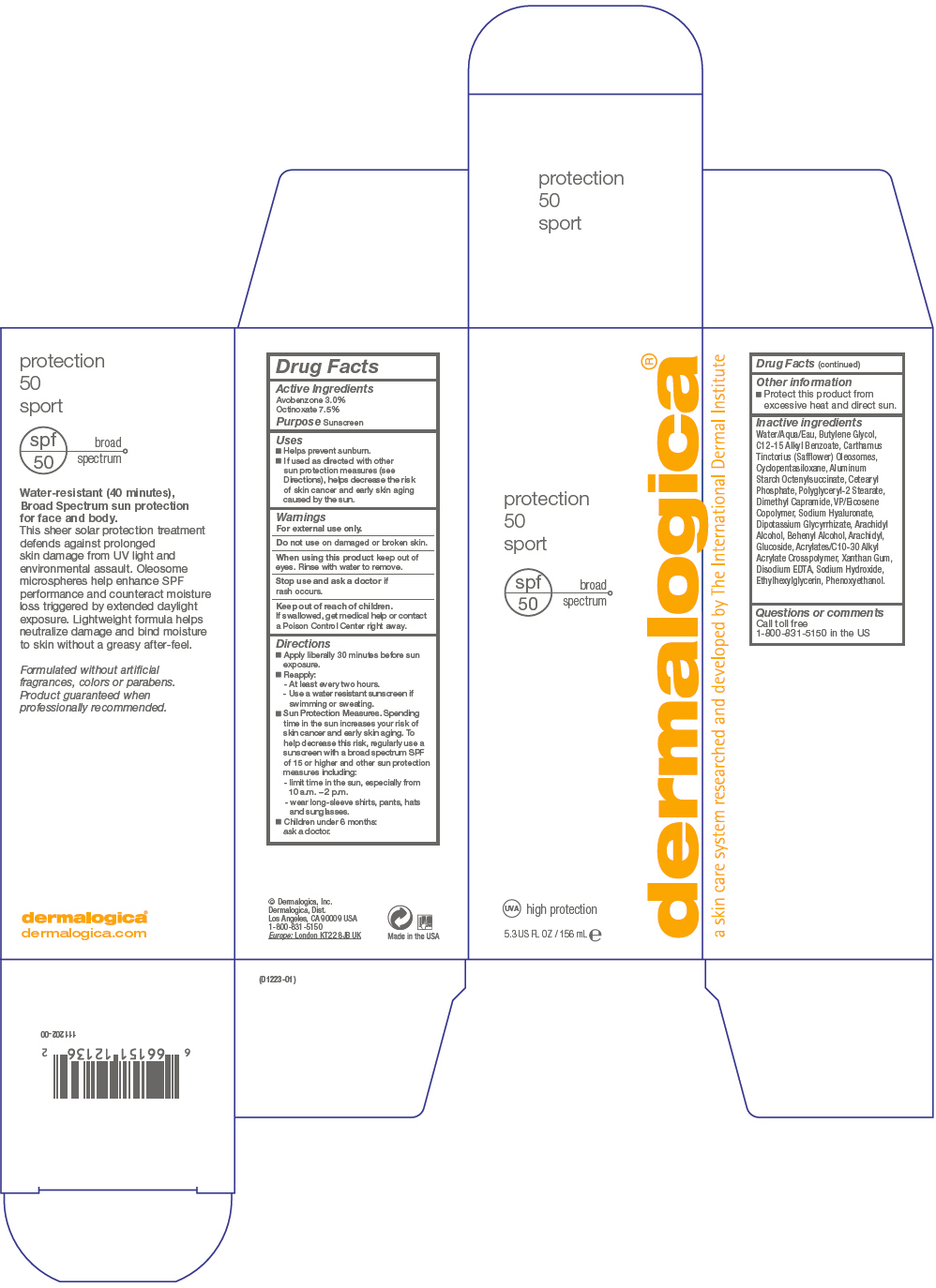 DRUG LABEL: Protection 50 Sport
NDC: 68479-012 | Form: LOTION
Manufacturer: Dermalogica, Inc.
Category: otc | Type: HUMAN OTC DRUG LABEL
Date: 20151112

ACTIVE INGREDIENTS: Avobenzone 30 mg/1 mL; Octinoxate 75 mg/1 mL
INACTIVE INGREDIENTS: Water; Butylene Glycol; Alkyl (C12-15) Benzoate; Carthamus Tinctorius Seed Oleosomes; Cyclomethicone 5; Aluminum Starch Octenylsuccinate; Cetearyl Phosphate; Dimethyl Capramide; Eicosyl Povidone; Hyaluronate Sodium; Glycyrrhizinate Dipotassium; Arachidyl Alcohol; Docosanol; Arachidyl Glucoside; Carbomer Interpolymer Type A (Allyl Sucrose Crosslinked); Xanthan Gum; Edetate Disodium; Sodium Hydroxide; Ethylhexylglycerin; Phenoxyethanol

Protection 50 Sport

Drug Facts

Active Ingredients

Avobenzone 3.0%

Octinoxate 7.5%

Purpose

Sunscreen

Uses

- Helps prevent sunburn.
- If used as directed with other sun protection measures (see Directions), helps decrease the risk of skin cancer and early skin aging caused by the sun.

Warnings

For external use only.

Do not use on damaged or broken skin.

When using this product keep out of eyes. Rinse with water to remove.

Stop use and ask a doctor if rash occurs.

Keep out of reach of children.

If swallowed, get medical help or contact a Poison Control Center right away.

Directions

- Apply liberally 30 minutes before sun exposure.
- Reapply:
  - At least every two hours.
  - Use a water resistant sunscreen if swimming or sweating.
- Sun Protection Measures. Spending time in the sun increases your risk of skin cancer and early skin aging. To help decrease this risk, regularly use a sunscreen with a broad spectrum SPF of 15 or higher and other sun protection measures including:
  - limit time in the sun, especially from 10 a.m. – 2 p.m.
  - wear long-sleeve shirts, pants, hats and sunglasses.
- Children under 6 months:
  ask a doctor.

Other information

- Protect this product from excessive heat and direct sun.

Inactive ingredients

Water/Aqua/Eau, Butylene Glycol, C12-15 Alkyl Benzoate, Carthamus Tinctorius (Safflower) Oleosomes, Cyclopentasiloxane, Aluminum Starch Octenylsuccinate, Cetearyl Phosphate, Polyglyceryl-2 Stearate, Dimethyl Capramide, VP/Eicosene Copolymer, Sodium Hyaluronate, Dipotassium Glycyrrhizate, Arachidyl Alcohol, Behenyl Alcohol, Arachidyl, Glucoside, Acrylates/C10-30 Alkyl Acrylate Crosspolymer, Xanthan Gum, Disodium EDTA, Sodium Hydroxide, Ethylhexylglycerin, Phenoxyethanol.

Questions or comments

Call toll free
1-800-831-5150 in the US

PRINCIPAL DISPLAY PANEL - 156 mL Tube Carton

protection
50
sport

spf
50

broad
spectrum

UVA high protection

5.3 US FL OZ / 156 mL e

dermalogica®